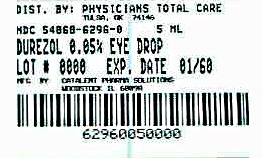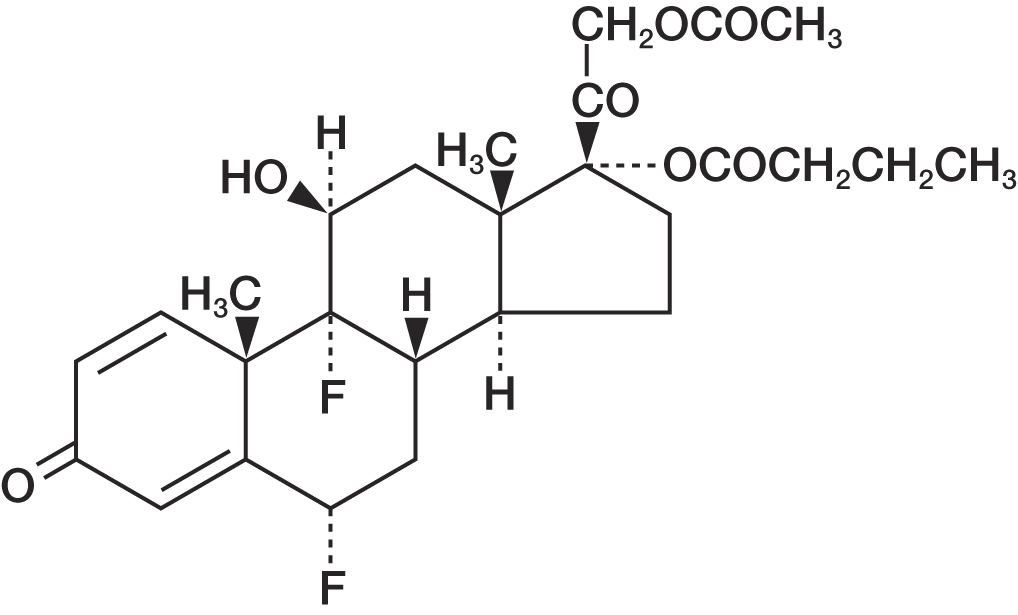 DRUG LABEL: DUREZOL
NDC: 54868-6296 | Form: EMULSION
Manufacturer: Physicians Total Care, Inc.
Category: prescription | Type: HUMAN PRESCRIPTION DRUG LABEL
Date: 20110128

ACTIVE INGREDIENTS: DIFLUPREDNATE 0.5 mg/1 mL
INACTIVE INGREDIENTS: BORIC ACID; CASTOR OIL; GLYCERIN; POLYSORBATE 80; WATER; SODIUM ACETATE; SODIUM HYDROXIDE

HIGHLIGHTS OF PRESCRIBING INFORMATION

These highlights do not include all the information needed to use Durezol® safely and effectively. See full prescribing information for Durezol.
DUREZOL® (difuprednate ophthalmic emulsion) 0.05%
Initial U.S. Approval: 2008

1 INDICATIONS AND USAGE

Durezol is a topical corticosteroid that is indicated for the treatment of inflammation and pain associated with ocular surgery. (1)

2 DOSAGE AND ADMINISTRATION

Instill one drop into the conjunctival sac of the affected eye(s) 4 times daily beginning 24 hours after surgery and continuing throughout the first 2 weeks of the postoperative period, followed by 2 times daily for a week and then a taper based on the response. (2)

3 DOSAGE STRENGTHS

Durezol contains 0.05% difluprednate, as a sterile preserved ophthalmic emulsion for topical ophthalmic use only. (3)

4 CONTRAINDICATIONS

Durezol, as with other ophthalmic corticosteroids, is contraindicated in most active viral diseases of the cornea and conjunctiva including epithelial herpes simplex keratitis (dendritic keratitis), vaccinia, and varicella, and also in mycobacterial infection of the eye and fungal diseases of ocular structures. (4)

5 WARNINGS AND PRECAUTIONS

• Intraocular pressure (IOP) increase-Prolonged use of corticosteroids may result in glaucoma with damage to the optic nerve, defects in visual acuity and fields of vision. If this product is used for 10 days or longer, IOP should be monitored. (5.1).

• Cataracts- Use of corticosteroids may result in posterior subcapsular cataract formation. (5.2)

• Delayed healing- The use of steroids after cataract surgery may delay healing and increase the

incidence of bleb formation. In those diseases causing thinning of the cornea or sclera, perforations have been known to occur with the use of topical steroids. The initial prescription and renewal of the medication order beyond 28 days should be made by a physician only after examination of the patient with the aid of magnification such as slit lamp biomicroscopy and, where appropriate, fluorescein staining. (5.3)

• Bacterial infections- Prolonged use of corticosteroids may suppress the host response and thus

increase the hazard of secondary ocular infections. In acute purulent conditions, steroids may mask infection or enhance existing infection. If signs and symptoms fail to improve after 2 days, the patient should be re-evaluated. (5.4)

• Viral infections- Employment of a corticosteroid medication in the treatment of patients with a history of herpes simplex requires great caution. Use of ocular steroids may prolong the course and may exacerbate the severity of many viral infections of the eye (including herpes simplex). (5.5)

• Fungal infections- Fungal infections of the cornea are particularly prone to develop coincidentally with long-term local steroid application. Fungus invasion must be considered in any persistent corneal ulceration where a steroid has been used or is in use. (5.6)

6 ADVERSE REACTIONS

To report SUSPECTED ADVERSE REACTIONS, contact Alcon Laboratories, Inc. at 1-800-757-9195 or FDA at 1-800-FDA-1088 or www.fda.gov/medwatch.

FULL PRESCRIBING INFORMATION

1 INDICATIONS AND USAGE

Durezol (difluprednate ophthalmic emulsion) 0.05%, a topical corticosteroid, is indicated for the treatment of inflammation and pain associated with ocular surgery.

2 DOSAGE AND ADMINISTRATION

Instill one drop into the conjunctival sac of the affected eye(s) 4 times daily beginning 24 hours after surgery and continuing throughout the first 2 weeks of the postoperative period, followed by 2 times daily for a week and then a taper based on the response.

3 DOSAGE STRENGTHS

Durezol contains 0.05% difluprednate as a sterile preserved emulsion for topical ophthalmic administration.

4 CONTRAINDICATIONS

The use of Durezol, as with other ophthalmic corticosteroids, is contraindicated in most active viral diseases of the cornea and conjunctiva including epithelial herpes simplex keratitis (dendritic keratitis), vaccinia, and varicella, and also in mycobacterial infection of the eye and fungal disease of ocular structures.

5 WARNINGS AND PRECAUTIONS

5.1 IOP Increase

Prolonged use of corticosteroids may result in glaucoma with damage to the optic nerve, defects in visual acuity and fields of vision. Steroids should be used with caution in the presence of glaucoma. If this product is used for 10 days or longer, intraocular pressure should be monitored.

5.2 Cataracts

Use of corticosteroids may result in posterior subcapsular cataract formation.

5.3 Delayed Healing

The use of steroids after cataract surgery may delay healing and increase the incidence of bleb formation. In those diseases causing thinning of the cornea or sclera, perforations have been known to occur with the use of topical steroids. The initial prescription and renewal of the medication order beyond 28 days should be made by a physician only after examination of the patient with the aid of magnification such as slit lamp biomicroscopy and, where appropriate, fluorescein staining.

5.4 Bacterial Infections

Prolonged use of corticosteroids may suppress the host response and thus increase the hazard of secondary ocular infections. In acute purulent conditions, steroids may mask infection or enhance existing infection. If signs and symptoms fail to improve after 2 days, the patient should be re-evaluated.

5.5 Viral Infections

Employment of a corticosteroid medication in the treatment of patients with a history of herpes simplex requires great caution. Use of ocular steroids may prolong the course and may exacerbate the severity of many viral infections of the eye (including herpes simplex).

5.6 Fungal Infections

Fungal infections of the cornea are particularly prone to develop coincidentally with long-term local steroid application. Fungus invasion must be considered in any persistent corneal ulceration where a steroid has been used or is in use. Fungal culture should be taken when appropriate.

5.7 Topical ophthalmic use only

Durezol is not indicated for intraocular administration.

6 ADVERSE REACTIONS

Adverse reactions associated with ophthalmic steroids include elevated intraocular pressure, which may be associated with optic nerve damage, visual acuity and field defects, posterior subcapsular cataract formation, secondary ocular infection from pathogens including herpes simplex, and perforation of the globe where there is thinning of the cornea or sclera.

Ocular adverse reactions occurring in 5-15% of subjects in clinical studies with Durezol included corneal edema, ciliary and conjunctival hyperemia, eye pain, photophobia, posterior capsule opacification, anterior chamber cells, anterior chamber _are, conjunctival edema, and blepharitis. Other ocular adverse reactions occurring in 1-5% of subjects included reduced visual acuity, punctate keratitis, eye inflammation, and iritis. Ocular adverse events occurring in < 1% of subjects included application site discomfort or irritation, corneal pigmentation and striae, episcleritis, eye pruritis, eyelid irritation and crusting, foreign body sensation, increased lacrimation, macular edema, scleral hyperemia, and uveitis. Most of these events may have been the consequence of the surgical procedure.

8 USE IN SPECIFIC POPULATIONS

8.1 Pregnancy

Teratogenic Effects

Pregnancy Category C. Difluprednate has been shown to be embryotoxic (decrease in embryonic body weight and a delay in embryonic ossification) and teratogenic (cleft palate and skeletal) anomalies when administered subcutaneously to rabbits during organogenesis at a dose of 1-10 μg/kg/day. The no-observed-effect-level (NOEL) for these effects was 1 μg/kg/day, and 10 μg/kg/day was considered to be a teratogenic dose that was concurrently found in the toxic dose range for fetuses and pregnant females. Treatment of rats with 10 μg/kg/day subcutaneously during organogenesis did not result in any reproductive toxicity, nor was it maternally toxic. At 100 μg/kg/day after subcutaneous administration in rats, there was a decrease in fetal weights and delay in ossification, and effects on weight gain in the pregnant females. It is difficult to extrapolate these doses of difluprednate to maximum daily human doses of Durezol, since Durezol is administered topically with minimal systemic absorption, and difluprednate blood levels were not measured in the reproductive animal studies. However, since use of difluprednate during human pregnancy has not been evaluated and cannot rule out the possibility of harm, Durezol should be used during pregnancy only if the potential benefit justifies the potential risk to the embryo or fetus.

8.3 Nursing Mothers

It is not known whether topical ophthalmic administration of corticosteroids could result in sufficient systemic absorption to produce detectable quantities in breast milk. Systemically administered corticosteroids appear in human milk and could suppress growth, interfere with endogenous corticosteroid production, or cause other untoward effects. Caution should be exercised when Durezol is administered to a nursing woman.

8.4 Pediatric Use

Safety and effectiveness in pediatric patients has not been established.

8.5 Geriatric Use

No overall differences in safety or effectiveness have been observed between elderly and younger patients.

11 DESCRIPTION

Durezol (difluprednate ophthalmic emulsion) 0.05% is a sterile, topical anti-inflammatory corticosteroid for ophthalmic use. The chemical name is 6α,9difluoro-11β,17,21-trihydroxypregna-1,4-diene-3,20-dione 21-acetate 17-butyrate (CAS number 23674-86-4). Difluprednate is represented by the following structural formula:

Difluprednate has a molecular weight of 508.56, and the empirical formula is C27H34F2O7.

Each mL contains: ACTIVE: difluprednate 0.5 mg (0.05%); INACTIVE: boric acid, castor oil, glycerin, polysorbate 80, water for injection, sodium acetate, sodium EDTA, sodium hydroxide (to adjust the pH to 5.2 to 5.8). The emulsion is essentially isotonic with a tonicity of 304 to 411 mOsm/kg. PRESERVATIVE: sorbic acid 0.1%.

12 CLINICAL PHARMACOLOGY

12.1 Mechanism of Action

Corticosteroids inhibit the inflammatory response to a variety of inciting agents that may delay or slow healing. They inhibit edema, fibrin deposition, capillary dilation, leukocyte migration, capillary proliferation, fibroblast proliferation, deposition of collagen, and scar formation associated with inflammation. There is no generally accepted explanation for the mechanism of action of ocular corticosteroids. However, corticosteroids are thought to act by the induction of phospholipase A2 inhibitory proteins, collectively called lipocortins. It is postulated that these proteins control the biosynthesis of potent mediators of in_ammation such as prostaglandins and leukotreines by inhibiting the release of their common precursor arachidonic acid. Arachidonic acid is released from membrane phospholipids by phospholipase A2.

Difluprednate is structurally similar to other corticosteroids.

12.3 Pharmacokinetics

Difluprednate undergoes deacetylation in vivo to 6α, 9-difluoroprednisolone 17-butyrate (DFB), an active metabolite of difluprednate.

Clinical pharmacokinetic studies of difluprednate after repeat ocular instillation of 2 drops of difluprednate (0.01% or 0.05%) QID for 7 days showed that DFB levels in blood were below the quantification limit (50 ng/mL) at all time points for all subjects, indicating the systemic absorption of difluprednate after ocular instillation of Durezol is limited.

13 NONCLINICAL TOXICOLOGY

13.1 Carcinogenesis, Mutagenesis, and Impairment of Fertility

Difluprednate was not genotoxic in vitro in the Ames test, and in cultured mammalian cells CHL/IU (a fibroblastic cell line derived from the lungs of newborn female Chinese hamsters). An in vivo micronucleus test of difluprednate in mice was also negative. Treatment of male and female rats with subcutaneous difluprednate up to 10 μg/kg/day prior to and during mating did not impair fertility in either gender. Long term studies have not been conducted to evaluate the carcinogenic potential of difluprednate.

13.2 Animal Toxicology and/or Pharmacology

In multiple studies performed in rodents and non-rodents, subchronic and chronic toxicity tests of difluprednate showed systemic effects such as suppression of body weight gain; a decrease in lymphocyte count; atrophy of the lymphatic glands and adrenal gland; and for local effects, thinning of the skin; all of which were due to the pharmacologic action of the molecule and are well known glucocorticosteroid effects. Most, if not all of these effects were reversible after drug withdrawal. The NOEL for the subchronic and chronic toxicity tests were consistent between species and ranged from 1-1.25 μg/kg per day.

14 CLINICAL STUDIES

14.1 Postoperative Ocular Inflammation and Pain

Clinical efficacy was evaluated in 2 randomized, double-masked, placebo-controlled trials in which subjects with an anterior chamber cell grade ≥ "2" (a cell count of 11 or higher) after cataract surgery were assigned to Durezol or placebo (vehicle) following surgery. One drop of Durezol or vehicle was self instilled either 2 (BID) or 4 (QID) times per day for 14 days, beginning the day after surgery. The presence of complete clearing (a cell count of 0) was assessed 8 and 15 days post-surgery using a slit lamp binocular microscope. In the intent-to-treat analyses of both studies, a signifocant benefit was seen in the QID Durezol-treated group in ocular inflammation and reduction of pain when compared with placebo. The consolidated clinical trial results are provided below.

Ocular Inflammation and Pain Endpoints (Studies Pooled)
 | Durezol QID N = 107 |  | Vehicle N = 220
Day | 8 | 15 | 8 | 15
Anterior Chamber cell clearing (% subjects) | 24 (22%)* | 44 (41%)* | 17 (7%) | 25 (11%)
Pain free (% subjects) | 62 (58%)* | 67 (63%)* | 59 (27%) | 76 (35%)
* Statistically significantly better than vehicle, p<0.01

16 HOW SUPPLIED/STORAGE AND HANDLING

Durezol (difluprednate ophthalmic emulsion) 0.05% is a sterile, aqueous topical ophthalmic emulsion supplied in an opaque plastic bottle with a controlled drop tip and a pink cap in the following size:

5 mL in a 5 mL bottle NDC 54868-6296-0.

Storage

Store at 15-25°C (59-77°F). Do not freeze. Protect from light. When not in use keep the bottles in the protective carton.

17 PATIENT COUNSELING INFORMATION

This product is sterile when packaged. Patients should be advised not to allow the dropper tip to touch any surface, as this may contaminate the emulsion. If pain develops or if redness, itching, or inflammation becomes aggravated, the patient should be advised to consult a physician. As with all ophthalmic preparations containing a preservative, patients should be advised not to wear contact lenses when using Durezol.

Revised: August 2010

U.S. Patent: 6,114,319

©2010 Alcon , Inc. ®

Manufactured for:

ALCON®

Alcon Laboratories, Inc.

6201 South Freeway

Fort Worth, Texas 76134 USA

1-800-757-9195

MedInfo@AlconLabs.com

Manufactured By:

Catalent Pharma Solutions

Woodstock, IL 60098

9005602-0810

Additional barcode labeling by:
Physicians Total Care, Inc.
Tulsa, OK 74146

PRINCIPAL DISPLAY PANEL

NDC 54868-6296-0

Rx Only

DUREZOL®

(difluprednate ophthalmic

Emulsion) 0.05%

Alcon®

5 mL

Sterile